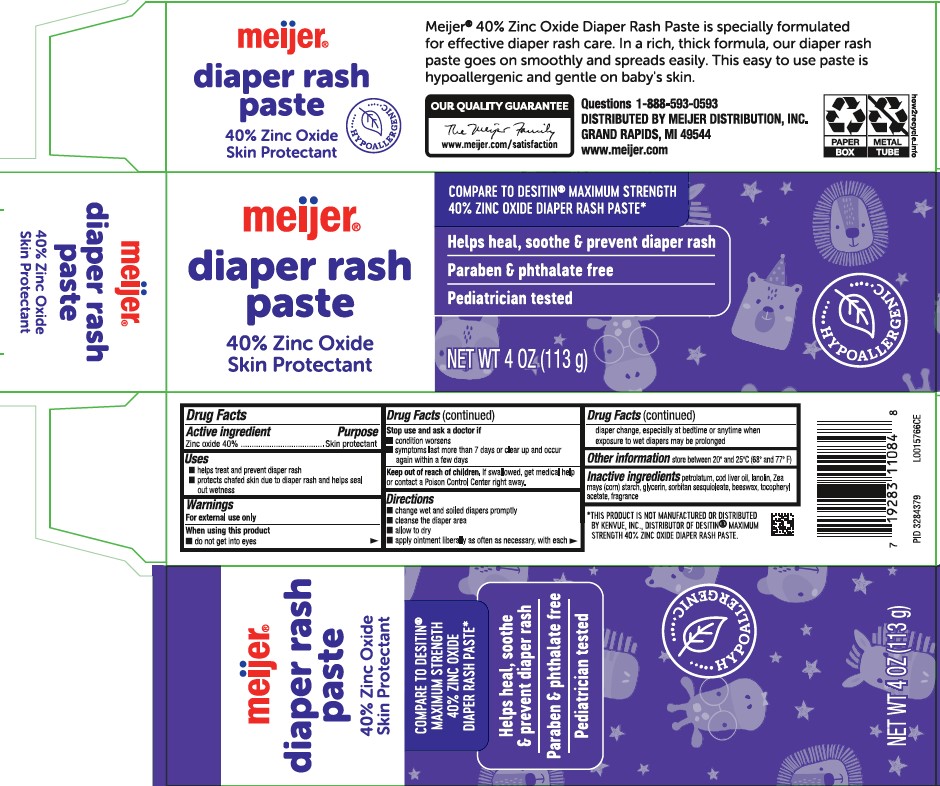 DRUG LABEL: Diaper Rash
NDC: 41250-412 | Form: PASTE
Manufacturer: Meijer, Inc.
Category: otc | Type: HUMAN OTC DRUG LABEL
Date: 20260219

ACTIVE INGREDIENTS: ZINC OXIDE 400 mg/1 g
INACTIVE INGREDIENTS: COD LIVER OIL; LANOLIN; STARCH, CORN; GLYCERIN; PETROLATUM; SORBITAN SESQUIOLEATE; YELLOW WAX; .ALPHA.-TOCOPHEROL ACETATE

Meijer 020.002/020AC-AD
Diaper Rash Ointment 40% Zinc Oxide

Active ingredient

Zinc oxide 40%

Purpose

Skin protectant

Uses

- helps treat and prevent diaper rash
- protects chafed skin due to diaper rash and helps seal out wetness

Warnings

For external use only

When using this product

- do not get into eyes

Stop use and ask a doctor if

- condition worsens
- symptoms last more than 7 days or clear up and occur again within a few days

Keep out of reach of children.

If swallowed, get medical help or contact a Poison Control Center right away.

Directions

- change wet and soilded diapers promptly
- cleanse the diaper area
- allow to dry
- apply ointment liberally as often as necessary, with each diaper change, especially at bedtime or anytime when exposure to wet diapers may be prolonged

Other information

store between 20⁰ and 25⁰C (68⁰ and 77⁰F)

Inactive ingredients

petrolatum, cod liver oil, lanolin, Zea mays (corn) starch, glycerin, sorbitan sesquioleate, beeswax, tocopheryl acetate, fragrance

Claims

meijer®

diaper rash paste

40% Zinc Oxide

Skin Protectant

HYPOALLERGENIC

Meijer® 40% Zinc Oxide Diaper Rash Paste is specially formulated for effective diaper rash care. In a rich, thick formula, our diaper rash paste goes on smoothly and spreads easily. This easy to use paste is hypoallergenic and gentle on baby's skin.

Disclaimer

*THIS PRODUCT IS NOT MANUFACTURED OR DISTRIBUTED BY KENVUE, INC., DISTRIBUTER OF DESTIN® MAXIMUM STRENGTH 40% ZINC OXIDE DIAPER RASH PASTE.

Adverse reaction

OUR QUALITY GUARENTEE

The Meijer Family

www.meijer.com/satisfaction

Questions 1-888-593-0593

DISTRIBUTED BY MEIJER DISTRIBUTION, INC

GRAND RAPIDS, MI 49544

www.meijer.com

Principal display panel

meijer®

diaper rash paste

40% Zinc Oxide

Skin Protectant

*Compare to Desitin Maximum Strength 40% Zinc Oxide Diaper Rash Paste*

Helps heal, soothe & prevent diaper rash

Paraben & Phthalate Free

Pediatrician tested

Hypoallergenic

NET WT. 4 OZ (113 g)